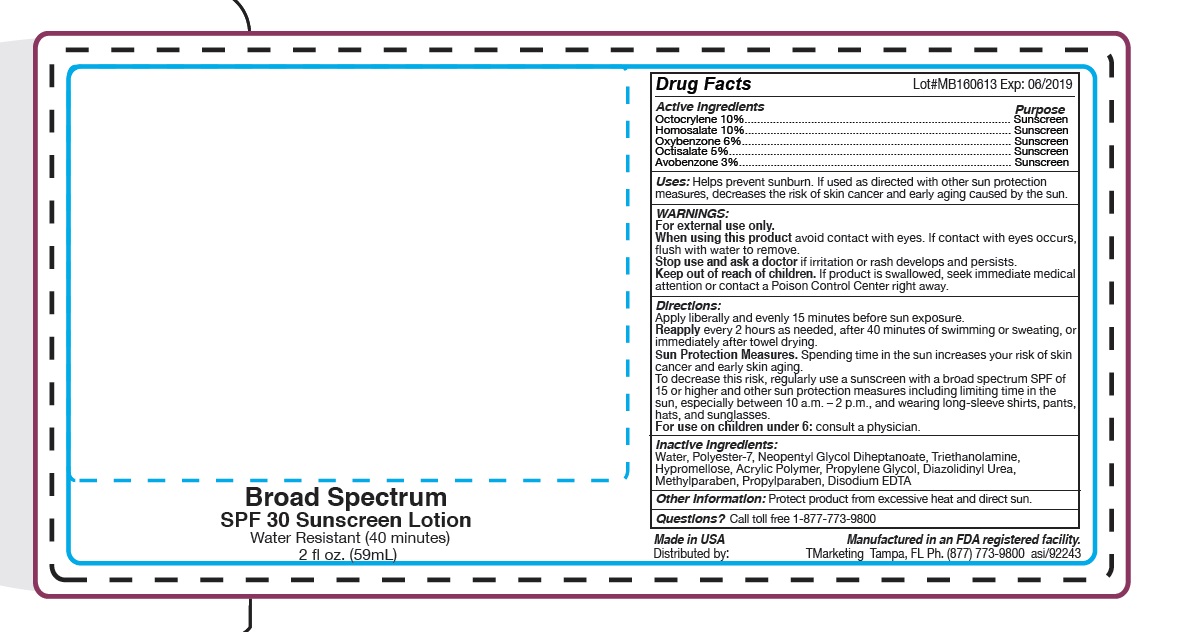 DRUG LABEL: Skin Crave Broad Spectrum spf30
NDC: 58418-224 | Form: LOTION
Manufacturer: Tropical Enterprises International Inc
Category: otc | Type: HUMAN OTC DRUG LABEL
Date: 20141205

ACTIVE INGREDIENTS: AVOBENZONE 3 mg/1 mL; OCTOCRYLENE 10 mg/1 mL; HOMOSALATE 10 mg/1 mL; OCTISALATE 5 mg/1 mL; OXYBENZONE 6 mg/1 mL
INACTIVE INGREDIENTS: WATER; POLYESTER-7; NEOPENTYL GLYCOL DIHEPTANOATE; HYPROMELLOSE 2208 (100 MPA.S); CUPRIC TRIETHANOLAMINE

Spf 30 Broad Spectrum Sunscreen - water based

DOSAGE AND ADMINISTRATION

Directions: Apply liberally and evenly 15 minutes before sun exposure.

Reapply every 2 hours as needed, after 40 minutes of swimming or sweating, or immediately after towel drying.

Inactive Ingredients:

Water, Polyester-7, Neopentyl Glycol Diheptanoate, Triethanolamine, Hypromellose, Acrylic Polymer, Propylene Glycol, Diazolidinyl Urea, Methylparaben, Propylparaben, Disodium EDTA

INDICATIONS AND USAGE

Uses: Helps prevent sunburn. If used as direted with other sun protection measures, decreases the risk of skin cancer and eraly aging caused by the sun.

Keep out of reach of children. If product is swallowed, seek immediate medical attention or contact a Poison Control Center right away.

Purpose: Sunscreen

WARNINGS:

For external use only.

When using this product avoid contact with eyes. If contact with eyes occurs, flush with water to remove.

Stop use and ask a doctor if irritation or rash develops and persists.

Keep out of reach of children. If products is swalled, seek immediate medical attention or contact a Poison Control Center right away.

Active Ingredients:

Octocrylene 10%

Homosalate 10%

Oxybenzone 6%

Octisalate 5%

Avobenzone 3%